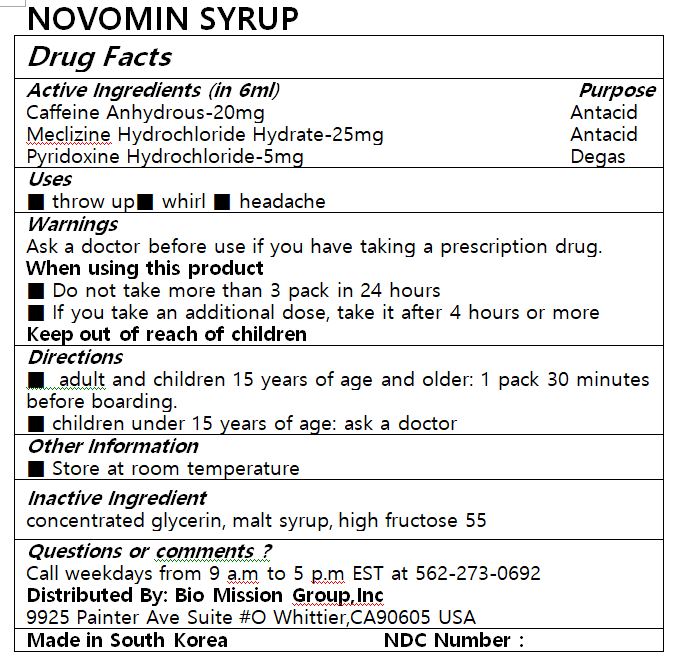 DRUG LABEL: NOVOMINSYRUP
NDC: 72988-0034 | Form: LIQUID
Manufacturer: Lydia Co., Ltd.
Category: otc | Type: HUMAN OTC DRUG LABEL
Date: 20230123

ACTIVE INGREDIENTS: CAFFEINE 20 mg/6 mL; MECLIZINE HYDROCHLORIDE 25 mg/6 mL; PYRIDOXINE HYDROCHLORIDE 5 mg/6 mL
INACTIVE INGREDIENTS: GLYCERIN

ACTIVE INGREDIENT

Caffeine Anhydrous, Meclizine Hydrochloride Hydrate, Pyridoxine Hydrochloride

PURPOSE

■ throw up■ whirl ■ headache

Keep out of reach of children

INDICATIONS AND USAGE

■ adult and children 15 years of age and older: 1 pack 30 minutes before boarding.

■ children under 15 years of age: ask a doctor

Ask a doctor before use if you have taking a prescription drug.

When using this product

■ Do not take more than 3 pack in 24 hours

■ If you take an additional dose, take it after 4 hours or more

Keep out of reach of children

INACTIVE INGREDIENT

concentrated glycerin, malt syrup, high fructose 55

DOSAGE AND ADMINISTRATION

for oral use